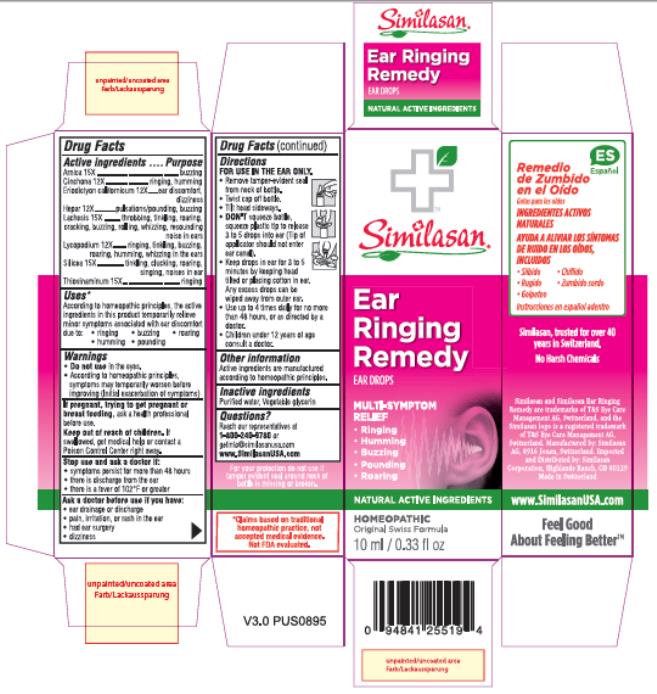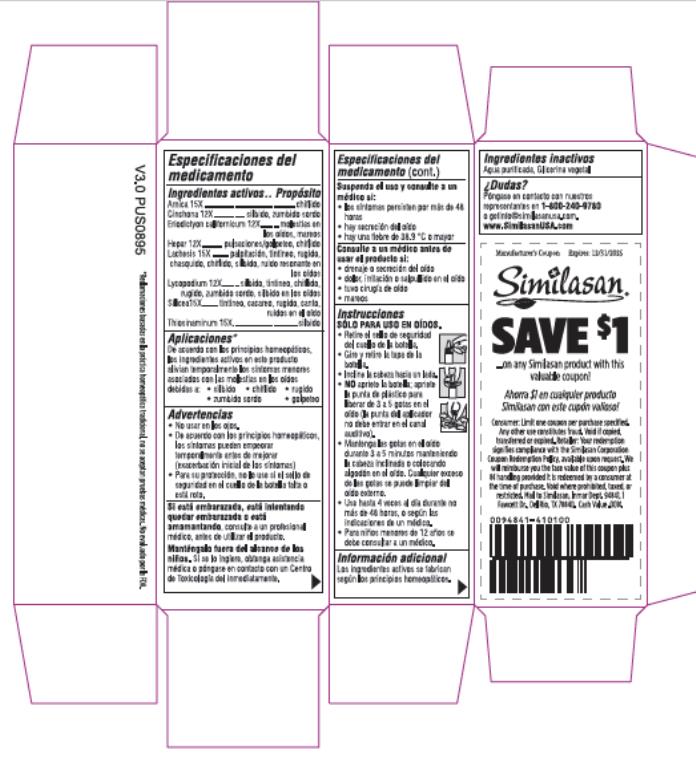 DRUG LABEL: Ear Ringing Remedy
NDC: 53799-275 | Form: SOLUTION
Manufacturer: Similasan AG
Category: homeopathic | Type: HUMAN OTC DRUG LABEL
Date: 20210311

ACTIVE INGREDIENTS: ARNICA MONTANA FLOWER 15 [hp_X]/10 mL; QUININE SULFATE 12 [hp_X]/10 mL; ERIODICTYON CALIFORNICUM LEAF 12 [hp_X]/10 mL; CALCIUM SULFIDE 12 [hp_X]/10 mL; LACHESIS MUTA VENOM 15 [hp_X]/10 mL; LYCOPODIUM CLAVATUM SPORE 12 [hp_X]/10 mL; SILICA DIMETHYL SILYLATE 15 [hp_X]/10 mL; ALLYLTHIOUREA 15 [hp_X]/10 mL
INACTIVE INGREDIENTS: WATER; GLYCERIN

Ear Ringing Remedy

Drug Facts

Active ingredients

Arnica 15X
Chininum sulphuricum12X
Eriodictyon californicum 12X
Hepar 12X
Lachesis 15X
Lycopodium 12X
Silica15X
Thiosinaminum 15X

Purpose

buzzing
ringing, humming
ear discomfort, dizziness
pulsations/pounding, buzzing
throbbing, tinkling, roaring, cracking, buzzing, rolling, whizzing, resounding noise in ears
ringing, tinkling, buzzing, roaring, humming, whizzing in the ears
tinkling, clucking, roaring, singing, noises in ear
ringing

Uses*

According to homeopathic principles, the active ingredients in this product temporarily relieve minor symptoms associated with ear discomfort due to:

• ringing • buzzing • roaring

• humming • pounding

Warnings

- Do not use in the eyes.
- According to homeopathic principles, symptoms may temporarily worsen before improving (Initial exacerbation of symptoms)

If pregnant, trying to get pregnant or breast feeding,

ask a health professional before use.

Keep out of reach of children.

If swallowed, get medical help or contact a Poison Control Center right away.

Stop use and ask a doctor if:

- symptoms persist for more than 48 hours
- there is discharge from the ear
- there is a fever of 102°F or greater

Ask a doctor before use if you have:

- ear drainage or discharge
- pain, irritation, or rash in the ear
- had ear surgery
- dizziness

Directions

FOR USE IN THE EAR ONLY.

- Remove tamper-evident seal from neck of bottle.
- Twist cap off bottle.
- Tilt head sideways.
- DON'T squeeze bottle, squeeze plastic tip to release 3 to 5 drops into ear (Tip of applicator should not enter ear canal).
- Keep drops in ear for 3 to 5 minutes by keeping head tilted or placing cotton in ear. Any excess drops can be wiped away from outer ear.
- Use up to 4 times daily for no more than 48 hours, or as directed by a doctor.
- Children under 12 years of age consult a doctor.

Other information

Active ingredients are manufactured according to homeopathic principles.

Inactive ingredient

Purified water, Vegetable glycerin

Questions?

Reach our representatives at 1-800-240-9780 or getinfo@similasanusa.com

www.SimilasanUSA.com

For your protection do not use if tamper evident seal around neck of bottle is missing or broken.

*Claims base on traditional homeopathic practice, not accepted medical evidence. Not FDA evaluated.

Principal Display Panel

Similasan
Ear Ringing Remedy
10 mL/ 0.33 fl oz